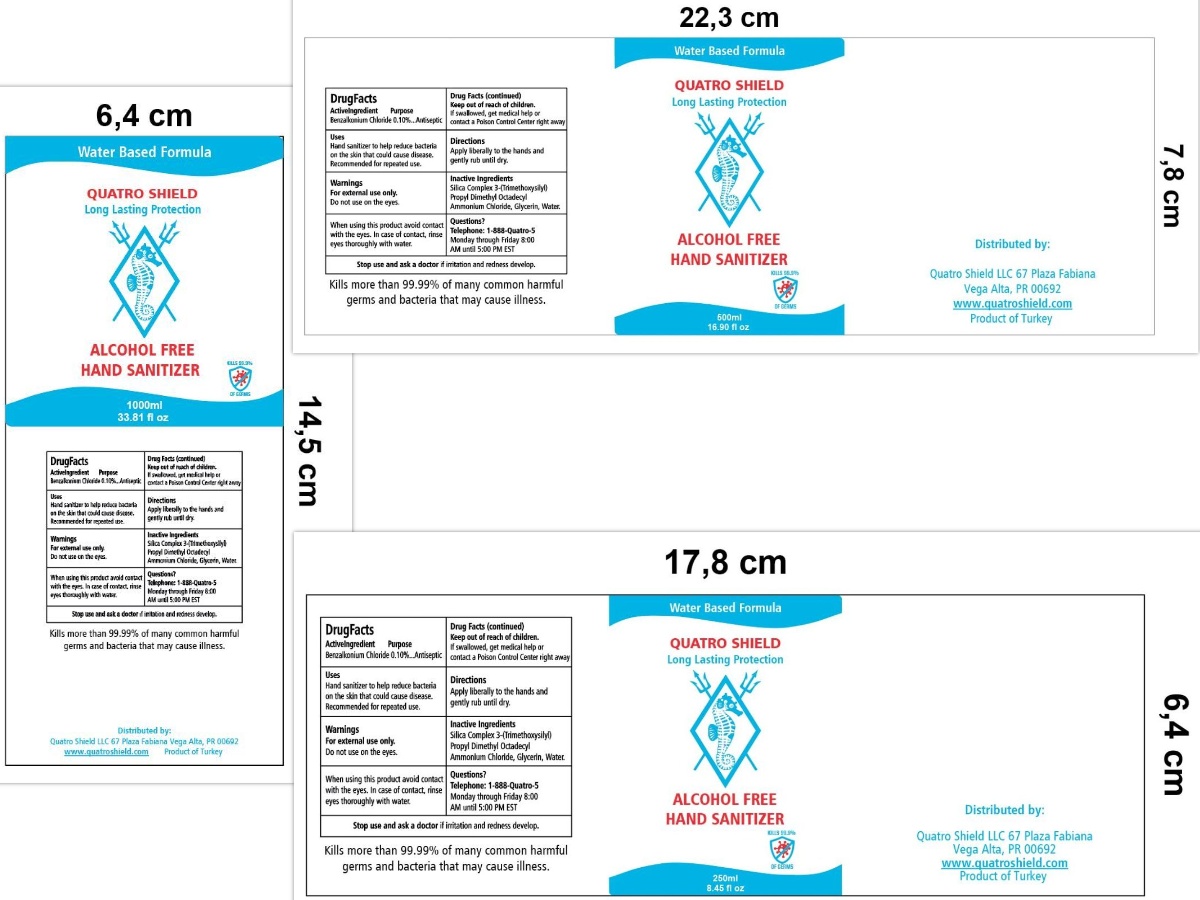 DRUG LABEL: QUATRO SHIELD HAND SANITIZER
NDC: 78873-609 | Form: LIQUID
Manufacturer: QUATRO SHIELD LLC
Category: otc | Type: HUMAN OTC DRUG LABEL
Date: 20200626

ACTIVE INGREDIENTS: BENZALKONIUM CHLORIDE 0.1 g/100 mL
INACTIVE INGREDIENTS: GLYCERIN; DIMETHYLOCTADECYL(3-(TRIMETHOXYSILYL)PROPYL)AMMONIUM CHLORIDE; WATER

Hand Sanitizer pump

Active Ingredient(s)

BENZALKONIUM CHLORIDE 0.10%

Purpose

Antiseptic

Use

HAND SANITIZER TO HELP REDUCE BACTERIA ON THE SKIN THAT COULD CAUSE DISEASE.

RECOMMENDED FOR REPEATED USE.

Warnings

FOR EXTERNAL USE ONLY

DO NOT USE ON THE EYES

WHEN USING THIS PRODUCT AVOID CONTACT WITH THE EYES. IN CASE OF CONTACT, RINSE EYES THOROUGH WITH WATER.

Stop use and ask a doctor if irritation and redness develop.

Keep out of reach of children. If swallowed, get medical help or contact a Poison Control Center right away.

Directions

- APPLY LIBERALLY TO THE HANDS AND GENTLY RUB UNTIL DRY.

Inactive ingredients

SILICA COMPLEX 3-(TRIMETHOXYSILYL) PROPYL DIMETHYL OCTADECYL AMMONIUM CHLORIDE, GLYCERIN, WATER

Package Label - Principal Display Panel

TELEPHONE: 1-888-QUATRO-5

MONDAY THROUGH FRIDAY 8:00 AM UNTIL 5:00 PM EST

WATER BASED FORMULA

QUATRO SHIELD

LONG-LASTING PROTECTION

ALCOHOL-FREE

HAND SANITIZER

KILLS 99.9% OF GERMS

Kills more than 99.99% of many common harmful germs and bacteria that may cause ilnness.

Distributed by:

Quatro Shield LLC

67 Plaza Fabiana

Vega Alta, PR 00692

www.Quatroshield.com

Product of Turkey